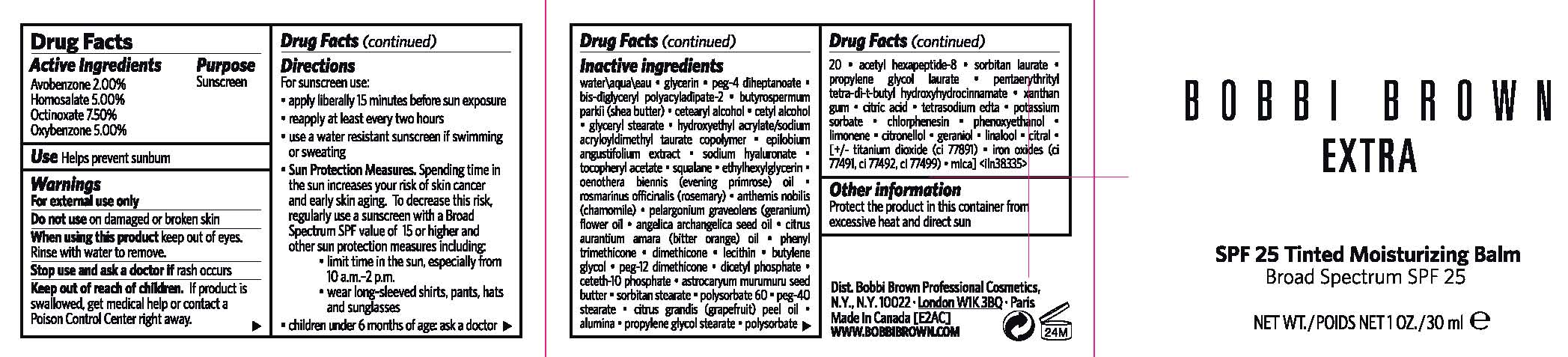 DRUG LABEL: BOBBI BROWN EXTRA
NDC: 64141-814 | Form: CREAM
Manufacturer: Bobbi Brown Professional Cosmetics Inc.
Category: otc | Type: HUMAN OTC DRUG LABEL
Date: 20120607

ACTIVE INGREDIENTS: OCTINOXATE 7.5 mL/100 mL; HOMOSALATE 5 mL/100 mL; OXYBENZONE 5 mL/100 mL; AVOBENZONE 2.0 mL/100 mL
INACTIVE INGREDIENTS: WATER; GLYCERIN; PEG-4 DIHEPTANOATE; SHEA BUTTER; CETOSTEARYL ALCOHOL; CETYL ALCOHOL; GLYCERYL MONOSTEARATE; EPILOBIUM ANGUSTIFOLIUM FLOWERING TOP; HYALURONATE SODIUM; .ALPHA.-TOCOPHEROL ACETATE; SQUALANE; EVENING PRIMROSE OIL; ROSEMARY; CHAMAEMELUM NOBILE FLOWER; PELARGONIUM GRAVEOLENS FLOWER OIL; ANGELICA SEED OIL; CITRUS AURANTIUM FRUIT OIL; PHENYL TRIMETHICONE; DIMETHICONE; LECITHIN, SOYBEAN; BUTYLENE GLYCOL; DIHEXADECYL PHOSPHATE; CETETH-10 PHOSPHATE; ASTROCARYUM MURUMURU SEED BUTTER; SORBITAN MONOSTEARATE; POLYSORBATE 60; PEG-40 STEARATE; CITRUS MAXIMA FRUIT RIND OIL; ALUMINUM OXIDE; PROPYLENE GLYCOL STEARATE; POLYSORBATE 20; ACETYL HEXAPEPTIDE-8; SORBITAN MONOLAURATE; PROPYLENE GLYCOL MONOLAURATE; PENTAERYTHRITOL TETRAKIS(3-(3,5-DI-TERT-BUTYL-4-HYDROXYPHENYL)PROPIONATE); XANTHAN GUM; CITRIC ACID MONOHYDRATE; EDETATE SODIUM; POTASSIUM SORBATE; CHLORPHENESIN; PHENOXYETHANOL; FERRIC OXIDE RED; MICA

DRUG FACTS

ACTIVE INGREDIENTS:

AVOBENZONE 2.00%

HOMOSALATE 5.00%

OCTINOXATE 7.50%

OXYBENZONE 5.00%

PURPOSE

SUNSCREEN

USE

HELPS PREVENT SUNBURN

WARNINGS

FOR EXTERNAL USE ONLY

Do not use on damaged or broken skin

When using this product keep out of eyes. Rinse with water to remove.

Stop use and ask a doctor if rash occurs

Keep out of reach of children.

If product is swallowed, get medical help or contact a Poison Control Center right away.

DIRECTIONS

For sunscreen use:
* apply liberally 15 minutes before sun exposure
* reapply at least every two hours
* use a water resistant sunscreen if swimming or sweating
* Sun Protection Measures.
Spending time in the sun increases your risk of skin cancer and early skin aging. To decrease this risk, regularly use a sunscreen with a Broad Spectrum SPF value of 15 or higher and other sun protection measures including:
o limit time in the sun, especially from 10 a.m.–2 p.m.
o wear long-sleeved shirts, pants, hats and sunglasses
* children under 6 months of age: ask a doctor

INACTIVE INGREDIENTS

INGREDIENTS: WATER\AQUA\EAU [] GLYCERIN [] PEG-4 DIHEPTANOATE [] BIS-DIGLYCERYL POLYACYLADIPATE-2 [] BUTYROSPERMUM PARKII (SHEA BUTTER) [] CETEARYL ALCOHOL [] CETYL ALCOHOL [] GLYCERYL STEARATE [] HYDROXYETHYL ACRYLATE/SODIUM ACRYLOYLDIMETHYL TAURATE COPOLYMER [] EPILOBIUM ANGUSTIFOLIUM EXTRACT [] SODIUM HYALURONATE [] TOCOPHERYL ACETATE [] SQUALANE [] ETHYLHEXYLGLYCERIN [] OENOTHERA BIENNIS (EVENING PRIMROSE) OIL [] ROSMARINUS OFFICINALIS (ROSEMARY) [] ANTHEMIS NOBILIS (CHAMOMILE) [] PELARGONIUM GRAVEOLENS (GERANIUM) FLOWER OIL [] ANGELICA ARCHANGELICA SEED OIL [] CITRUS AURANTIUM AMARA (BITTER ORANGE) OIL [] PHENYL TRIMETHICONE [] DIMETHICONE [] LECITHIN [] BUTYLENE GLYCOL [] PEG-12 DIMETHICONE [] DICETYL PHOSPHATE [] CETETH-10 PHOSPHATE [] ASTROCARYUM MURUMURU SEED BUTTER [] SORBITAN STEARATE [] POLYSORBATE 60 [] PEG-40 STEARATE [] CITRUS GRANDIS (GRAPEFRUIT) PEEL OIL [] ALUMINA [] PROPYLENE GLYCOL STEARATE [] POLYSORBATE 20 [] ACETYL HEXAPEPTIDE-8 [] SORBITAN LAURATE [] PROPYLENE GLYCOL LAURATE [] PENTAERYTHRITYL TETRA-DI-T-BUTYL HYDROXYHYDROCINNAMATE [] XANTHAN GUM [] CITRIC ACID [] TETRASODIUM EDTA [] POTASSIUM SORBATE [] CHLORPHENESIN [] PHENOXYETHANOL [] LIMONENE [] CITRONELLOL [] GERANIOL [] LINALOOL [] CITRAL [] [+/- TITANIUM DIOXIDE (CI 77891) [] IRON OXIDES (CI 77491, CI 77492, CI 77499) [] MICA

OTHER INFORMATION

protect the product in this container from excessive heat and direct sun

PACKAGE LABEL

BOBBI BROWN

EXTRA

SPF 25 TINTED MOISTURIZING BALM

BROAD SPECTRUM SPF 25

NET WT./ POIDS NT 1 OZ/ 30 ML

DIST. BOBBI BROWN PROFESSIONAL COSMETICS

NY, NY 10022